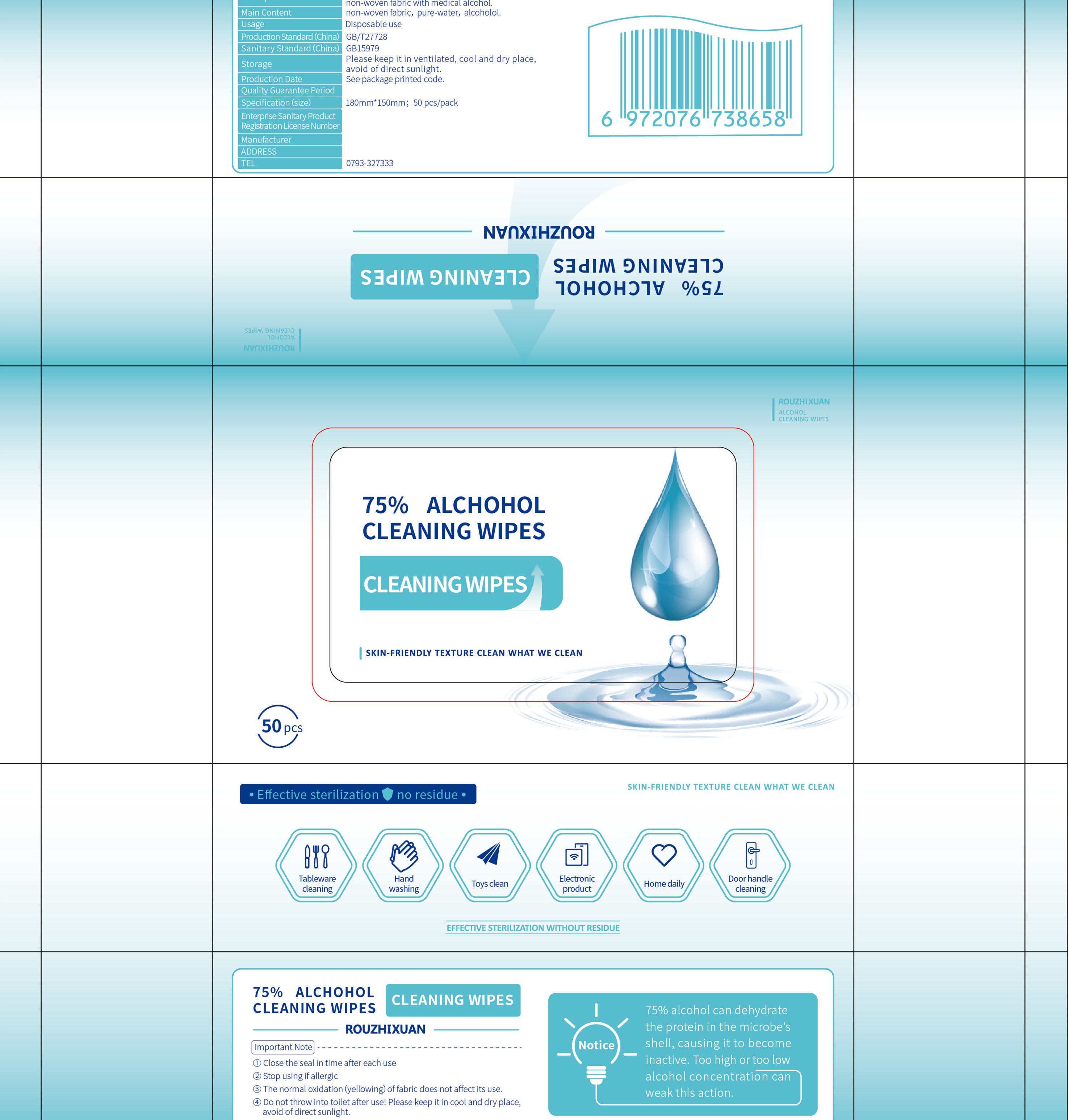 DRUG LABEL: Wet Tissue with Alcohol 75%
NDC: 40905-002 | Form: CLOTH
Manufacturer: Jiangxi Hualida Industrial Co., Ltd.
Category: otc | Type: HUMAN OTC DRUG LABEL
Date: 20200513

ACTIVE INGREDIENTS: ALCOHOL 20 mL/50 1
INACTIVE INGREDIENTS: CETRIMONIUM; GLYCERIN; POLYGLYCERIN-6; PROPYLENE GLYCOL; PHENOXYETHANOL; DIRECT BLACK 19; WATER; POLYESTER (ADIPIC ACID, 1,6-HEXANEDIOL, NEOPENTYL GLYCOL)

DOSAGE AND ADMINISTRATION

Don't put it in the light。

INACTIVE INGREDIENT

Quaternary ammonium salt compounds such as cetyl ammonium,

propylene glycol

glycerol,

phenoxyethanol

ethyl,

hexyl glycerol

hydrogen peroxide,

water, viscose

polyester

INDICATIONS AND USAGE

Wipe gently with wet tissues on hands。

ACTIVE INGREDIENT

Alcohol

keep out of children

PURPOSE

Disinfection
Sterilization
No Rinseing

WARNINGS

1.Close the seal in time after each use Stop using if allergic
2.The normal oxidation lyellowing) of fabric does not affect its use.
3.Do not throw into toilet after use!

4.Please keep it in cool and dry place,avoid of direct sunlight.